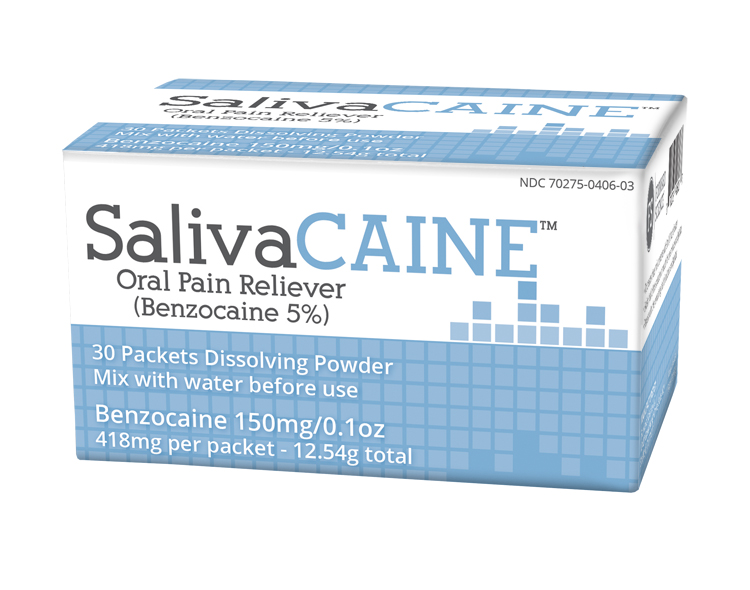 DRUG LABEL: SalivaCAINE
NDC: 70275-406 | Form: POWDER, FOR SOLUTION
Manufacturer: Forward Science Technologies LLC
Category: otc | Type: HUMAN OTC DRUG LABEL
Date: 20200117

ACTIVE INGREDIENTS: BENZOCAINE 150 mg/3000 mg
INACTIVE INGREDIENTS: SODIUM PHOSPHATE, DIBASIC, ANHYDROUS; SODIUM CHLORIDE; SILICON DIOXIDE; CALCIUM CHLORATE DIHYDRATE; SODIUM PHOSPHATE, MONOBASIC, ANHYDROUS

SalivaCAINE

Active ingredient

Benzocaine 5% (w/v)

Purpose: oral pain reliever

Uses

For temporary relief of occasional minor oral
irritation, oral pain, and sore mouth.

METHEMOGLOBINEMIA WARNING

Use of this product may cause methemoglobinemia, a serious condition that must be treated promptly
because it reduces the amount of oxygen carried in blood. This can occur even if you have used this
product before. Stop use and seek immediate medical attention if you or a child in your care develops:

• pale, gray, or blue colored skin (cyanosis)
• headache • dizziness or lightheadedness
• rapid heart rate • shortness of breath
• fatigue or lack of energy

Allergy alert

Do not use this product if you have a history of allergy to local anesthetics such as procaine,
butacaine, benzocaine, or any other ‘caine’ anesthetics. If a skin reaction occurs, stop use and seek
medical help right away.

Sore throat warning

If sore throat is severe, persists for more than
2 days, is accompanied or followed by fever
headache, rash, nausea, or vomiting, consult a
doctor promptly. If sore mouth symptoms do
not improve in 7 days, see your dentist or
doctor promptly.

Do Not Use

• for teething

• in children under 2 years of age

Keep out of reach of children

Directions

Adults and children 2 years of age and older:

Mix packet with 0.1oz water and apply the rinse to the affected area. Gargle, swish around in the mouth, or allow to remain in place 1 minute then Spit Out.
Use up to 4 times daily or as directed by a dentist or doctor. Children under 12 years of age should be supervised in the use of the product.

Children under 2 years of age: do not use

Inactive ingredients

Calcium Chloride, Dibasic Sodium Phosphate, Monobasic Sodium
Phosphate, Silicon Dioxide, Sodium Chloride

Questions

Call 1-855-696-7254 (M - F 8:30 - 5:30 CST)
You may also report side effects to this phone number.

PURPOSE

oral pain reliever

PACKAGE LABEL

NDC 70275-0406-03

SalivaCAINE

Oral Pain Reliever

(Benzocaine 5%)

30 Packets Dissolving Powder

Mix with water before use

Benzocaine 150mg/0.1oz

418mg per packet - 12.54g total